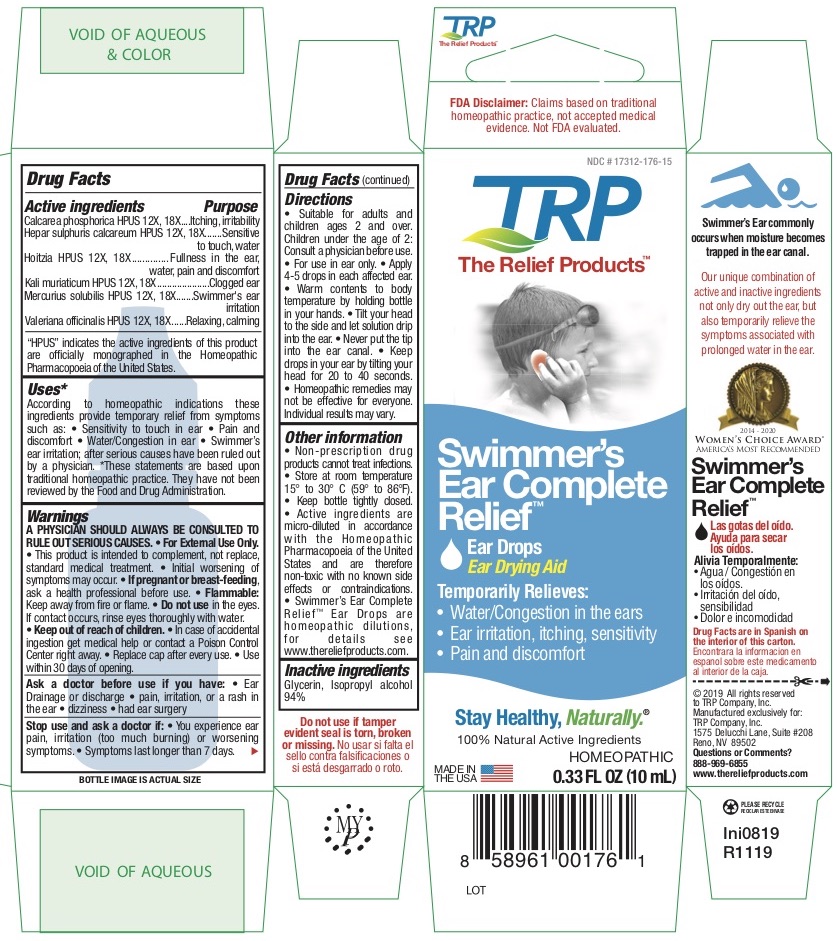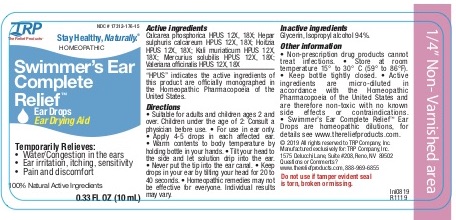 DRUG LABEL: Swimmers Ear Complete Relief
NDC: 17312-176 | Form: LIQUID
Manufacturer: TRP Company
Category: homeopathic | Type: HUMAN OTC DRUG LABEL
Date: 20251215

ACTIVE INGREDIENTS: POTASSIUM CHLORIDE 12 [hp_X]/1 mL; CALCIUM SULFIDE 13 [hp_X]/1 mL; TRIBASIC CALCIUM PHOSPHATE 12 [hp_X]/1 mL; SILICON DIOXIDE 13 [hp_X]/1 mL; VALERIAN 6 [hp_X]/1 mL; LOESELIA MEXICANA TOP 12 [hp_X]/1 mL; MERCURIUS SOLUBILIS 12 [hp_X]/1 mL
INACTIVE INGREDIENTS: ALCOHOL; GLYCERIN

Swimmer’s Ear Complete Relief ™

ACTIVE INGREDIENT

Calcarea phosphorica HPUS 12X, 18X...............Itching, irritability
Hepar sulphuris calcareum HPUS 12X, 18X.......Sensitive to touch, water
Hoitzia HPUS 12X, 18X.......................................Fullness in the ear, water, pain and discomfort
Kali muriaticum HPUS 12X, 18X ........................Clogged ear
Mercurius solubilis HPUS 12X, 18X....................Swimmer's ear irritation
Valeriana officinalis HPUS 12X, 18X...................Relaxing, calming

"HPUS" indicates the active ingredients are in the Homeopathic Pharmacopoeia of the United States.

PURPOSE

Calcarea phosphorica HPUS - Itching, irritability
Hepar sulphuris calcareum HPUS - Sensitive to touch, water
Hoitzia HPUS - Fullness in the ear, water, pain and discomfort
Kali muriaticum HPUS - Clogged ear
Mercurius solubilis HPUS - Swimmer's ear irritation
Valeriana officinalis HPUS - Relaxing, calming

Uses:*
According to homeopathic indications these ingredients provide temporary relief from symptoms such as: • Sensitivity to touch in ear • Pain and discomfort • Water/Congestion in ear • Swimmer’s ear irritation; after serious causes have been ruled out by a physician.
*These statements are based upon traditional homeopathic practice. They have not been reviewed by the Food and Drug Administration.

Warnings:

A PHYSICIAN SHOULD ALWAYS BE CONSULTED TO RULE OUT SERIOUS CAUSES. For External Use Only.

- This product is intended to complement, not replace, standard medical treatment.
- Initial worsening of symptoms may occur.

Flammable: Keep away from fire or flame.

PREGNANCY OR BREAST FEEDING

If pregnant or breast-feeding, ask a health professional before use.

Do not use: in the eyes. If contact occurs, rinse eyes thoroughly with water

Keep out of reach of children

In case of accidental ingestion, get medical help or contact a Poison Control Center right away.

DOSAGE AND ADMINISTRATION

Directions:• Suitable for adults and children ages 2 and over. Children under the age of 2: Consult a physician before use. • For use in ear only. • Apply 4-5 drops in each affected ear. • Warm contents to body temperature by holding bottle in your hands. • Tilt your head to the side and let solution drip into the ear. • Never put the tip into the ear canal. • Keep drops in your ear by tilting your head for 20 to 40 seconds. • Homeopathic remedies may not be effective for everyone. Individual results may vary.

Other information:

• Non-prescription drug products cannot treat infections. • Store at room temperature 15° to 30° C (59° to 86°F). • Keep bottle tightly closed. • Active ingredients are micro-diluted in accordance with the Homeopathic Pharmacopoeia of the United States and are therefore non-toxic with no known side effects or contraindications. • Swimmer’s Ear Complete ReliefTM Ear Drops are homeopathic dilutions, for details see www.thereliefproducts.com.

Inactive Ingredients:
Glycerin, Isopropyl alcohol 94%

Stop Use

Stop use and ask a doctor if: •You experience ear pain, irritation (too much burning) or worsening symptoms. • Your symptoms last longer than 7 days

Ask doctor

Ask a doctor before use if you have: • Ear Drainage or discharge • pain, irritation, or a rash in the ear • dizziness • had ear surgery

PACKAGE LABEL

FDA Disclaimer: Claims based on traditional homeopathic practice, not accepted medical evidence. Not FDA evaluated.